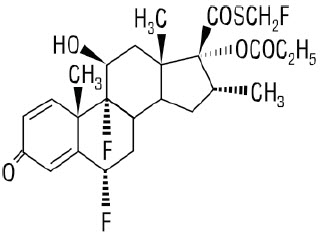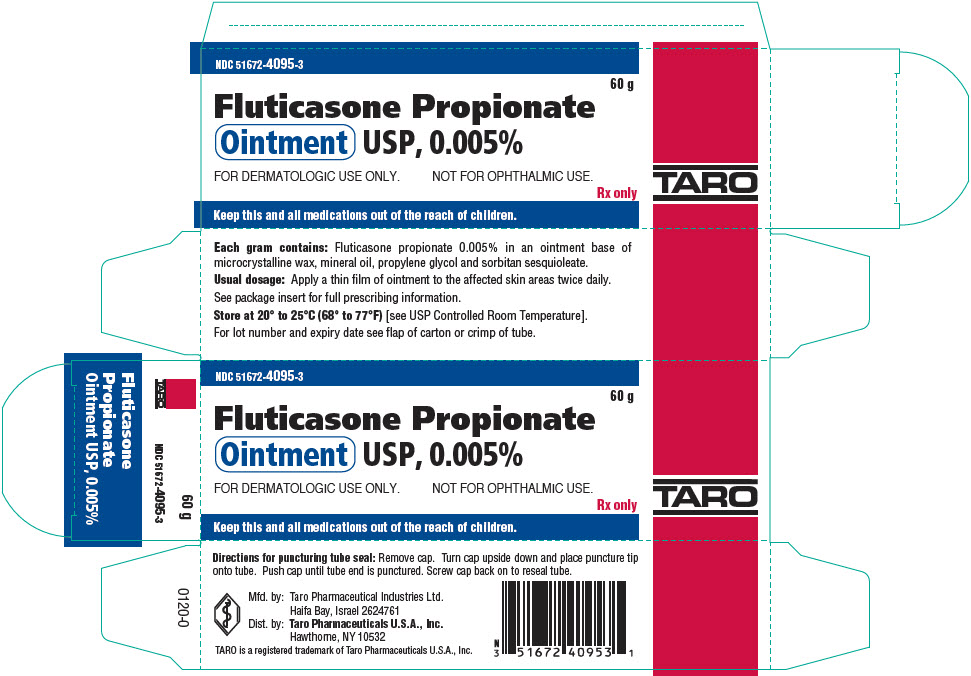 DRUG LABEL: Fluticasone Propionate
NDC: 51672-4095 | Form: OINTMENT
Manufacturer: Taro Pharmaceuticals U.S.A., Inc.
Category: prescription | Type: HUMAN PRESCRIPTION DRUG LABEL
Date: 20241219

ACTIVE INGREDIENTS: FLUTICASONE PROPIONATE 0.05 mg/1 g
INACTIVE INGREDIENTS: MINERAL OIL; MICROCRYSTALLINE WAX; SORBITAN SESQUIOLEATE; PROPYLENE GLYCOL

HIGHLIGHTS OF PRESCRIBING INFORMATION

These highlights do not include all the information needed to use FLUTICASONE PROPIONATE OINTMENT safely and effectively. See full prescribing information for FLUTICASONE PROPIONATE OINTMENT.
FLUTICASONE PROPIONATE ointment, for topical use
Initial U.S. Approval: 1990

1 INDICATIONS AND USAGE

Fluticasone propionate ointment is a corticosteroid indicated for the relief of the inflammatory and pruritic manifestations of corticosteroid-responsive dermatoses in adult patients. (1)

2 DOSAGE AND ADMINISTRATION

- Apply a thin film to affected skin areas twice daily. (2)

3 DOSAGE FORMS AND STRENGTHS

Ointment, 0.005%, supplied in 5 g physician samples, 15 g, 30 g and 60 g tubes. (3)

4 CONTRAINDICATIONS

Fluticasone propionate ointment is contraindicated in those patients with a history of serious hypersensitivity to any of the components in the preparation. (4)

5 WARNINGS AND PRECAUTIONS

- Hypothalamic-Pituitary-Adrenal (HPA) Axis Suppression: Reversible HPA axis suppression and resulting clinical glucocorticoid insufficiency can occur during or after withdrawal of treatment. Risk factors include use over large surface area, prolonged use, use under occlusion, altered skin barrier, liver failure, and young age. Modify use if HPA axis suppression is suspected. (5.1)

6 ADVERSE REACTIONS

The most common adverse reactions (<1%) were pruritus, burning, hypertrichosis, increased erythema, urticaria, irritation, and lightheadedness. (6.1)

To report SUSPECTED ADVERSE REACTIONS, contact Taro Pharmaceuticals U.S.A., Inc., at 1-866-923-4914 or FDA at 1-800-FDA-1088 or www.fda.gov/medwatch.

FULL PRESCRIBING INFORMATION

1 INDICATIONS AND USAGE

Fluticasone propionate ointment is a corticosteroid indicated for the relief of the inflammatory and pruritic manifestations of corticosteroid-responsive dermatoses in adult patients.

2 DOSAGE AND ADMINISTRATION

Apply a thin film of fluticasone propionate ointment to the affected skin areas twice daily. Rub in gently.

Avoid use with occlusive dressing.

Fluticasone propionate ointment is for topical use only; it is not for ophthalmic, oral or intravaginal use.

3 DOSAGE FORMS AND STRENGTHS

Ointment, 0.005%. Each gram of Fluticasone Propionate Ointment USP, 0.005% contains 0.05 mg fluticasone propionate in a white to off-white translucent ointment base. Fluticasone propionate ointment is supplied in 5 g physician samples, 15 g, 30 g and 60 g tubes.

4 CONTRAINDICATIONS

Fluticasone propionate ointment is contraindicated in those patients with a history of hypersensitivity to any of the components in the preparation.

5 WARNINGS AND PRECAUTIONS

5.1 Hypothalamic-Pituitary-Adrenal (HPA) Axis Suppression and Other Adverse Endocrine Effects

Topical corticosteroids, including fluticasone propionate ointment, can produce reversible HPA axis suppression with the potential for clinical glucocorticoid insufficiency. Factors that predispose to HPA axis suppression include large treatment surface areas, prolonged use, use under occlusion, altered skin barrier, liver failure, and young age. Cushing's syndrome, hyperglycemia, and unmasking of latent diabetes mellitus can also result from systemic absorption of topical corticosteroids.

If HPA axis suppression is suspected, gradually withdraw the drug, reduce the frequency of application, or substitute with a less potent corticosteroid. An ACTH stimulation test may be helpful in evaluating patients for HPA axis suppression.

Pediatric patients may be at greater risk of HPA axis suppression due to their higher skin surface area to body mass ratios [ see Use in Specific Populations (8.4)].

HPA axis suppression may occur during or after withdrawal of treatment. If HPA axis suppression is suspected, gradually withdraw the drug, reduce the frequency of application, or substitute with a less potent corticosteroid. Evaluation of HPA axis suppression may be done by using the cosyntropin stimulation test.

5.2 Local Adverse Reactions

Fluticasone propionate ointment may cause local adverse reactions, including skin atrophy [ see Adverse Reactions (6.1, 6.2)]. The risk is greater with use under occlusion.

5.3 Allergic Contact Dermatitis

Allergic contact dermatitis with topical corticosteroids is usually diagnosed by observing failure to heal rather than noting a clinical exacerbation. Such an observation can be corroborated with appropriate diagnostic patch testing. Discontinue fluticasone propionate ointment if appropriate.

5.4 Skin Infections

If concomitant skin infections are present or develop, use an appropriate antimicrobial. If a favorable response does not occur promptly, discontinue use of fluticasone propionate ointment until the infection has been adequately controlled.

6 ADVERSE REACTIONS

The following adverse reactions are discussed in greater detail in other sections of the labeling:

- HPA Axis Suppression and Other Adverse Endocrine Effects [ see Warnings and Precautions (5.1)]
- Local Adverse Reactions [ see Warnings and Precautions (5.2)]
- Concomitant Skin Infections [ see Warnings and Precautions (5.3)]

6.1 Clinical Trials Experience

Because clinical trials are conducted under widely varying conditions, adverse reaction rates observed in the clinical trials of a drug cannot be directly compared to rates in the clinical trials of another drug and may not reflect the rates observed in practice.

In controlled clinical trials, the total incidence of adverse reactions associated with the use of fluticasone propionate ointment was approximately 4%. These adverse reactions were usually mild, self-limiting, and consisted primarily of pruritus, burning, hypertrichosis, increased erythema, urticaria, irritation, and lightheadedness. Each of these events occurred individually in less than 1% of patients.

6.2 Postmarketing Experience

The following local adverse reactions have been identified during post-approval use of fluticasone propionate ointment: acneiform dermatitis, edema, rash, hypoaesthesia, pustular psoriasis, skin atrophy.

The following systemic adverse reactions have been identified during post-approval use of fluticasone propionate cream and fluticasone propionate ointment: immunosuppression/ Pneumocystis jiroveciipneumonia/leukopenia/thrombocytopenia; hyperglycemia/glycosuria; Cushing syndrome; generalized body edema/blurred vision; and acute urticarial reaction (edema, urticaria, pruritus, and throat swelling).

The following local adverse reactions have also been reported with the use of topical corticosteroids: telangiectasia, striae, dryness, folliculitis, hypopigmentation, perioral dermatitis, allergic contact dermatitis, secondary infection, and miliaria.

Because these reactions are reported voluntarily from a population of uncertain size, it is not always possible to reliably estimate their frequency or establish a causal relationship to drug exposure.

8 USE IN SPECIFIC POPULATIONS

8.1 Pregnancy

TERATOGENIC EFFECTS

Pregnancy Category C

There are no adequate and well-controlled studies in pregnant women. Therefore, fluticasone propionate ointment should be used during pregnancy only if the potential benefit justifies the potential risk to the fetus.

Systemic embryofetal development studies were conducted in mice, rats and rabbits.

Subcutaneous doses of 15 μg/kg/day, 45 μg/kg/day and 150 μg/kg/day of fluticasone propionate were administered to pregnant female mice from gestation days 6 to 15. A teratogenic effect characteristic of corticosteroids (cleft palate) was noted after administration of 45 μg/kg/day and 150 μg/kg/day (less than the MRHD in adults based on body surface area comparisons) in this study. No treatment related effects on embryofetal toxicity or teratogenicity were noted at 15 μg/kg/day (less than the MRHD in adults based on body surface area comparisons).

Subcutaneous doses of 10 μg/kg/day, 30 μg/kg/day and 100 μg/kg/day of fluticasone propionate were administered to pregnant female rats in two embryofetal development studies (one study administered fluticasone propionate from gestation days 6 to 15 and the other study from gestation days 7 to 17). In the presence of maternal toxicity, fetal effects noted at 100 μg/kg/day (less than the MRHD in adults based on body surface area comparisons) included decreased fetal weights, omphalocele, cleft palate, and retarded skeletal ossification. No treatment related effects on embryofetal toxicity or teratogenicity were noted at 10 μg/kg/day (less than the MRHD in adults based on body surface area comparisons).

Subcutaneous doses of 0.08 μg/kg/day, 0.57 μg/kg/day and 4 μg/kg/day of fluticasone propionate were administered to pregnant female rabbits from gestation days 6 to 18. Fetal effects noted at 4 μg/kg/day (less than the MRHD in adults based on body surface area comparisons) included decreased fetal weights, cleft palate and retarded skeletal ossification. No treatment related effects on embryofetal toxicity or teratogenicity were noted at 0.57 μg/kg/day (less than the MRHD in adults based on body surface area comparisons).

Oral doses of 3 μg/kg/day, 30 μg/kg/day and 300 μg/kg/day fluticasone propionate were administered to pregnant female rabbits from gestation days 8 to 20. No fetal or teratogenic effects were noted at oral doses up to 300 μg/kg/day (less than the MRHD in adults based on body surface area comparisons) in this study. However, no fluticasone propionate was detected in the plasma in this study, consistent with the established low bioavailability following oral administration.

Fluticasone propionate crossed the placenta following administration of a subcutaneous or an oral dose of 100 μg/kg tritiated fluticasone propionate to pregnant rats.

8.3 Nursing Mothers

Systemically administered corticosteroids appear in human milk and can suppress growth, interfere with endogenous corticosteroid production, or cause other untoward effects. It is not known whether topical administration of corticosteroids could result in sufficient systemic absorption to produce detectable quantities in human milk. Because many drugs are excreted in human milk, caution should be exercised when fluticasone propionate ointment is administered to a nursing woman.

8.4 Pediatric Use

The safety and effectiveness of fluticasone propionate ointment have not been established in pediatric patients. Use of fluticasone propionate ointment in pediatric patients is not recommended.

Because of a higher ratio of skin surface area to body mass, pediatric patients are at a greater risk than adults of systemic effects when treated with topical drugs. They are, therefore, also at greater risk of HPA axis suppression and adrenal insufficiency upon the use of topical corticosteroids [ see Warnings and Precautions (5.1)].

In a trial of 35 pediatric subjects treated with fluticasone propionate ointment, 0.005% for atopic dermatitis over at least 35% of body surface area, subnormal adrenal function was observed with cosyntropin stimulation testing at the end of 3 to 4 weeks of treatment in 4 subjects who had normal testing prior to treatment. It is not known if these subjects had recovery of adrenal function because follow-up testing was not performed. The decreased responsiveness of cosyntropin testing was not correlated to age of subject, amount of fluticasone propionate ointment used, or serum levels of fluticasone propionate.

In the above trial, telangiectasia on the face was noted in one subject on the eighth day of a 4-week treatment period. Facial use was discontinued and the telangiectasia resolved.

HPA axis suppression, Cushing's syndrome, linear growth retardation, delayed weight gain, and intracranial hypertension have been reported in pediatric patients receiving topical corticosteroids.

8.5 Geriatric Use

A limited number of patients above 65 years of age (n = 203) have been treated with futicasone propionate ointment in US and non-US clinical trials. No overall differences in safety or effectiveness were observed between these subjects and younger subjects, and other reported clinical experience has not identified differences in responses between the elderly and younger patients. However, greater sensitivity of some older individuals cannot be ruled out.

11 DESCRIPTION

Fluticasone Propionate Ointment USP, 0.005% contains fluticasone propionate [ S-Fluoromethyl 6α, 9α-difluoro-11β-hydroxy-16α-methyl-3-oxo-17α-propionyloxyandrosta-1,4-diene-17β-carbothioate], a synthetic fluorinated corticosteroid, for topical use.

Chemically, fluticasone propionate is C25H31F3O5S. It has the following structural formula:

Fluticasone propionate has a molecular weight of 500.6. It is a white to off-white powder and is insoluble in water.

Each gram of Fluticasone Propionate Ointment USP, 0.005% contains fluticasone propionate 0.05 mg in a white to off-white translucent ointment base of microcrystalline wax, mineral oil, propylene glycol and sorbitan sesquioleate.

12 CLINICAL PHARMACOLOGY

12.1 Mechanism of Action

Corticosteroids play a role in cellular signaling, immune function, inflammation, and protein regulation; however, the precise mechanism of action of fluticasone propionate ointment in corticosteroid-responsive dermatoses is unknown.

12.2 Pharmacodynamics

Vasoconstrictor Assay

Studies performed with fluticasone propionate ointment indicate that it is in the medium range of potency as demonstrated in vasoconstrictor trials in healthy subjects when compared with other topical corticosteroids. However, similar blanching scores do not necessarily imply therapeutic equivalence.

12.3 Pharmacokinetics

Absorption

The extent of percutaneous absorption of topical corticosteroids is determined by many factors, including the vehicle and the integrity of the epidermal barrier. Occlusive dressing enhances penetration. Topical corticosteroids can be absorbed from normal intact skin. Inflammation and/or other disease processes in the skin increase percutaneous absorption.

In a study of 6 healthy subjects applying 25 g of fluticasone propionate ointment 0.005% twice daily to the trunk and legs for up to 5 days under occlusion, plasma levels of fluticasone ranged from 0.08 to 0.22 ng/mL.

Distribution

The percentage of fluticasone propionate bound to human plasma proteins averaged 91%. Fluticasone propionate is weakly and reversibly bound to erythrocytes. Fluticasone propionate is not significantly bound to human transcortin.

Metabolism

No metabolites of fluticasone propionate were detected in an in vitrostudy of radiolabeled fluticasone propionate incubated in human skin homogenate.

Fluticasone propionate is metabolized in the liver by cytochrome P450 3A4-mediated hydrolysis of the 5-fluoromethyl carbothioate grouping. This transformation occurs in 1 metabolic step to produce the inactive 17-β-carboxylic acid metabolite, the only known metabolite detected in man. This metabolite has approximately 2,000 times less affinity than the parent drug for the glucocorticoid receptor of human lung cytosol in vitroand negligible pharmacological activity in animal studies. Other metabolites detected in vitrousing cultured human hepatoma cells have not been detected in man.

13 NONCLINICAL TOXICOLOGY

13.1 Carcinogenesis, Mutagenesis, Impairment of Fertility

In an oral (gavage) mouse carcinogenicity study, doses of 0.1 mg/kg/day, 0.3 mg/kg/day and 1 mg/kg/day fluticasone propionate were administered to mice for 18 months. Fluticasone propionate demonstrated no tumorigenic potential at oral doses up to 1 mg/kg/day (less than the MRHD in adults based on body surface area comparisons) in this study.

In a dermal mouse carcinogenicity study, 0.05% fluticasone propionate ointment (40 μl) was topically administered for 1, 3 or 7 days/week for 80 weeks. Fluticasone propionate demonstrated no tumorigenic potential at dermal doses up to 6.7 μg/kg/day (less than the MRHD in adults based on body surface area comparisons) in this study.

Fluticasone propionate revealed no evidence of mutagenic or clastogenic potential based on the results of five in vitrogenotoxicity tests (Ames assay, E. coli fluctuation test, S. cerevisiae gene conversion test, Chinese hamster ovary cell chromosome aberration assay and human lymphocyte chromosome aberration assay) and one in vivogenotoxicity test (mouse micronucleus assay).

No evidence of impairment of fertility or effect on mating performance was observed in a fertility and general reproductive performance study conducted in male and female rats at subcutaneous doses up to 50 μg/kg/day (less than the MRHD in adults based on body surface area comparisons).

16 HOW SUPPLIED/STORAGE AND HANDLING

Fluticasone Propionate Ointment USP, 0.005% is a white to off-white translucent ointment supplied as follows:

5 g tubes (physician samples, tubes only) | NDC 51672-4095-5
15 g tubes | NDC 51672-4095-1
30 g tubes | NDC 51672-4095-2
60 g tubes | NDC 51672-4095-3

STORAGE AND HANDLING

Store at 20° to 25°C (68° to 77°F)[see USP Controlled Room Temperature].

17 PATIENT COUNSELING INFORMATION

Advise the patient to read the FDA-approved patient labeling (Patient Information).

Advise the patient:

- Avoid contact with the eyes.
- Do not bandage the treated skin area, or cover or wrap it to cause occlusion unless directed by the healthcare provider.
- Report any signs of local adverse reaction to their healthcare provider.
- Do not use on the face, underarms, or groin areas unless directed by the healthcare provider.

Manufactured by: Taro Pharmaceutical Industries Ltd., Haifa Bay, Israel 2624761
Distributed by: Taro Pharmaceuticals U.S.A., Inc.,Hawthorne, NY 10532
Revised: January 2020

PATIENT INFORMATION
Fluticasone Propionate (floo tik' a sone proe' pee oh nate) Ointment, 0.005%

Important: Fluticasone propionate ointment is for use on skin only (topical).Do not get fluticasone propionate ointment near or in your eyes, mouth, or vagina.
Read this Patient Information before you start using fluticasone propionate ointment and each time you get a refill. There may be new information. This information does not take the place of talking to your healthcare provider about your medical condition or your treatment.

What is fluticasone propionate ointment?
Fluticasone propionate ointment is a prescription corticosteroid medicine used on the skin (topical) for the relief of inflammation and itching caused by certain skin conditions in adults.
It is not known if fluticasone propionate ointment is safe and effective in children. Fluticasone propionate ointment is not recommended for use in children.

Before using fluticasone propionate ointment, tell your healthcare provider about all of your medical conditions, including if you:

- have an allergy to any of the ingredients in fluticasone propionate ointment
- have a skin infection at the site to be treated. You may also need medicine to treat the skin infection.
- have adrenal gland problems
- have liver problems
- have diabetes
- have thinning skin (atrophy) at the site to be treated
- are pregnant or plan to become pregnant. It is not known if fluticasone propionate ointment will harm your unborn baby.
- are breastfeeding or plan to breastfeed. It is not known if fluticasone propionate ointment can pass into your breast milk and harm your baby.

Tell your healthcare provider about all the medicines you take,including prescription and over-the-counter medicines, vitamins, and herbal supplements. Especially tell your healthcare provider if you take other corticosteroid medicines by mouth or use other products on your skin that contain corticosteroids.

How should I use fluticasone propionate ointment?

- Use fluticasone propionate ointment exactly as your healthcare provider tells you to use it.
- Apply a thin film of fluticasone propionate ointment to the affected area 2 times each day. Gently rub into your skin.
- Do not bandage, cover, or wrap the treated area unless your healthcare provider tells you to.
- Do not use fluticasone propionate ointment on your face, groin, underarms (armpits), unless your healthcare provider tells you to.
- Wash your hands after applying fluticasone propionate ointment, unless your hands are being treated.
- Tell your healthcare provider if your symptoms get worse with fluticasone propionate ointment or if your symptoms do not improve after 2 weeks of treatment.

What are the possible side effects of fluticasone propionate ointment?
Fluticasone propionate ointment may cause serious side effects, including:

- Fluticasone propionate ointment can pass through your skin and maycause adrenal gland problems. This is more likely to happen if you use fluticasone propionate ointment for too long, use it over a large treatment area, use it with other topical medicines that contain corticosteroids, cover the treated area, or have liver failure. Your healthcare provider may do blood tests to check your adrenal gland function during and after treatment with fluticasone propionate ointment.
- Skin problems, including skin reactions or thinning of your skin (atrophy), skin infections, and allergic reactions(allergic contact dermatitis) at the treatment site. Tell your healthcare provider if you get any skin reactions such as pain, tenderness, swelling, or healing problems.

The most common side effects of fluticasone propionate ointmentinclude itching, burning, excessive hair growth, skin redness, hives, and lightheadedness.
These are not all the possible side effects of fluticasone propionate ointment. Call your doctor for medical advice about side effects. You may report side effects to FDA at 1-800-FDA-1088.

How should I store fluticasone propionate ointment?

- Store fluticasone propionate ointment between 68°F to 77°F (20°C to 25°C).

Keep fluticasone propionate ointment and all medicines out of the reach of children.

General information about the safe and effective use of fluticasone propionate ointment.
Medicines are sometimes prescribed for purposes other than those listed in a Patient Information leaflet. Do not use fluticasone propionate ointment for a condition for which it was not prescribed. Do not give fluticasone propionate ointment to other people, even if they have the same symptoms you have. It may harm them. You can ask your pharmacist or healthcare provider for information about fluticasone propionate ointment that is written for health professionals.

What are the ingredients in fluticasone propionate ointment?
Active ingredient: fluticasone propionate
Inactive ingredients:microcrystalline wax, mineral oil, propylene glycol and sorbitan sesquioleate
Manufactured by: Taro Pharmaceutical Industries Ltd., Haifa Bay, Israel 2624761
Distributed by: Taro Pharmaceuticals U.S.A., Inc.,Hawthorne, NY 10532

This Patient Information has been approved by the U.S. Food and Drug Administration.

Revised: January 2020

PRINCIPAL DISPLAY PANEL - 60 g Tube Carton

NDC 51672-4095-3

60 g

Fluticasone Propionate
Ointment USP, 0.005%

FOR DERMATOLOGIC USE ONLY.
NOT FOR OPHTHALMIC USE.

Rx only

Keep this and all medications out of the reach of children.

TARO